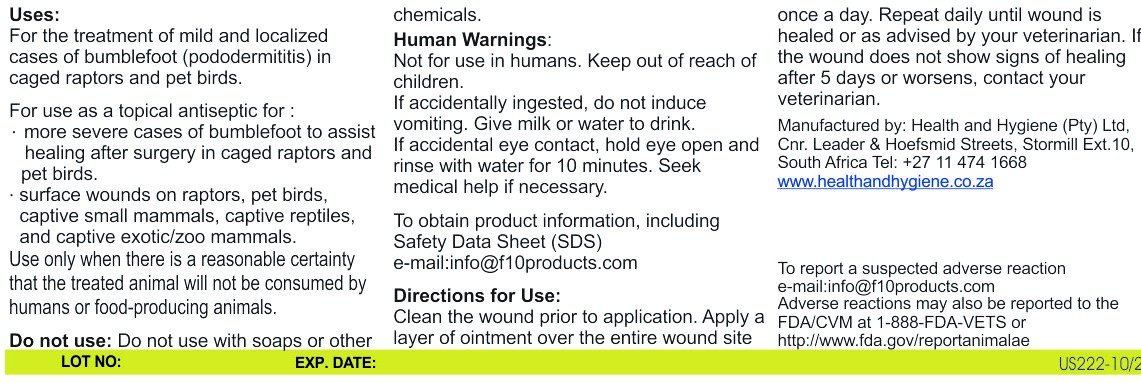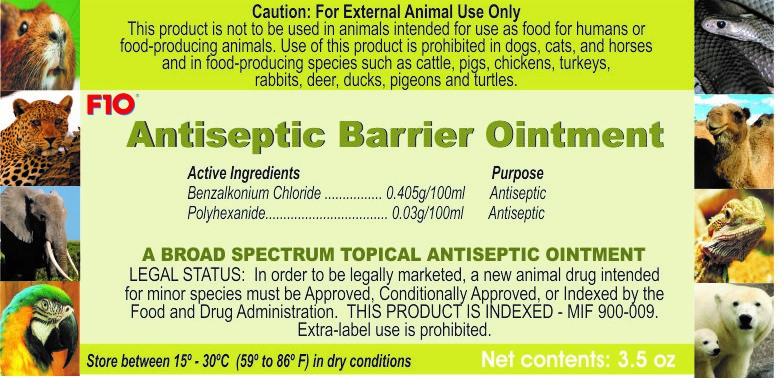 DRUG LABEL: F10
NDC: 86152-0091 | Form: OINTMENT
Manufacturer: Health and Hygiene (Pty) Ltd
Category: animal | Type: OTC ANIMAL DRUG LABEL
Date: 20220128

ACTIVE INGREDIENTS: BENZALKONIUM CHLORIDE 0.4 g/100 g; BIGUANIDE 0.03 g/100 g

F10 Antiseptic Barrier Ointment

Warnings

Not for use in humans. Keep out of reach of children

Uses

For the treatment of mild and localized cases of bumblefoot.

For the use as a topical antiseptic for:

-severe cases of bumblefoot

Surface wounds

Direction of Use

Clean the wound prior to application. Apply a layer of ointment over the entire wound site once a day. repeat daily until wound is healed or as adviced by veterinarian.

Packaging Label

Front Panel

US222-10 20 Antiseptic Barrier ointment 100g FP.jpg

Packaging Label

Back Panel

US222-10 20 Antiseptic Barrier ointment 100g BP.jpg